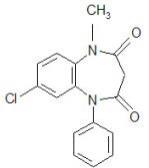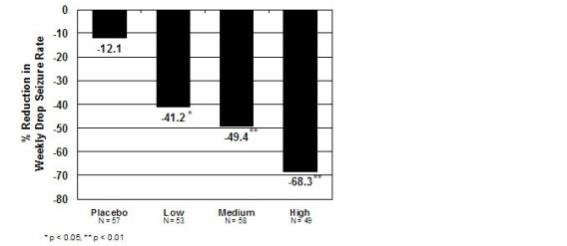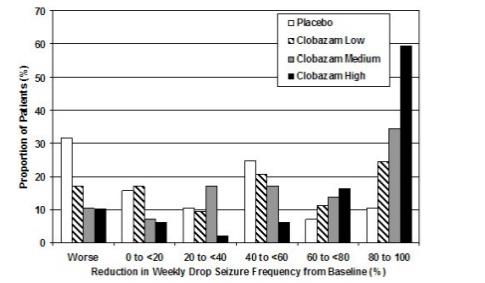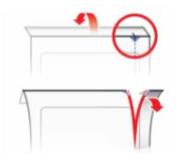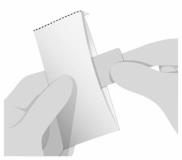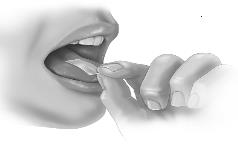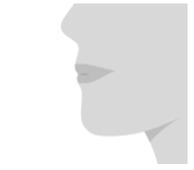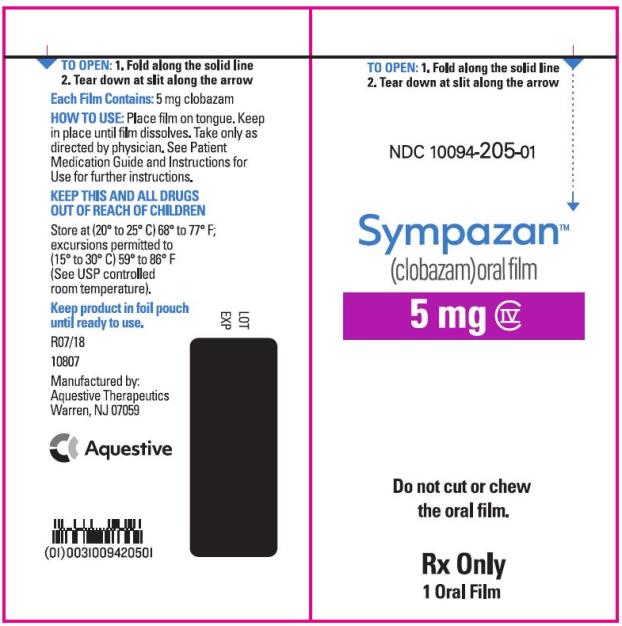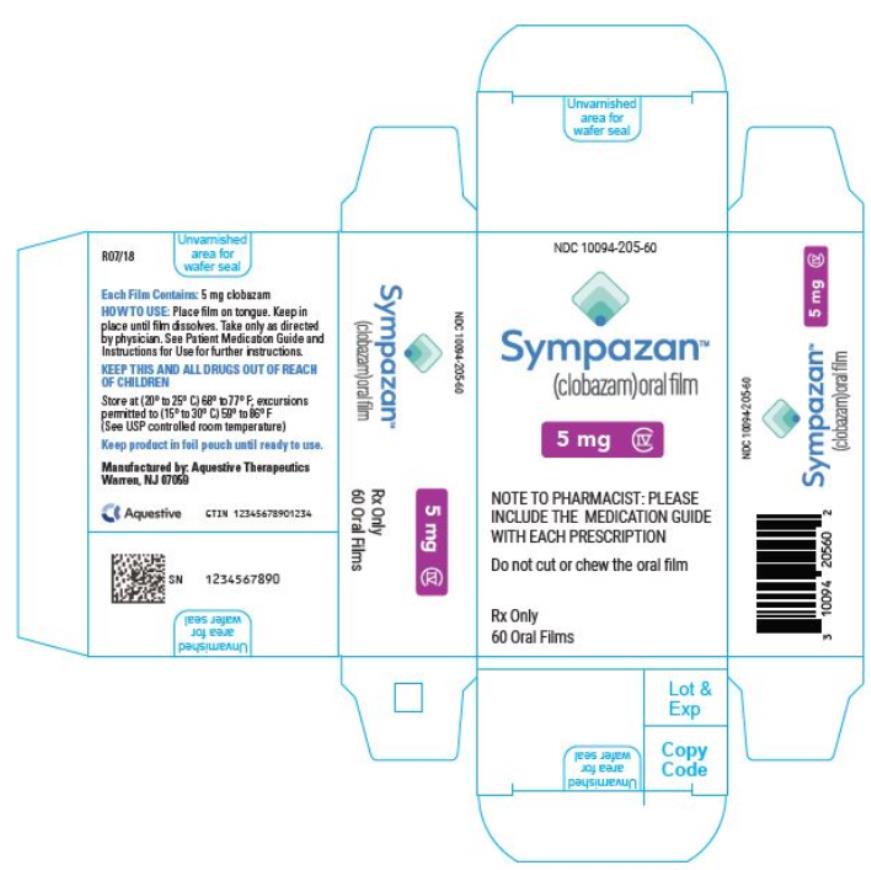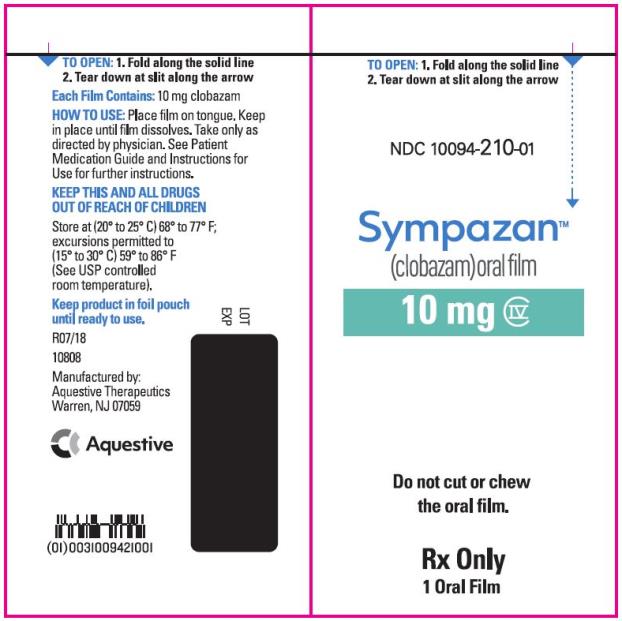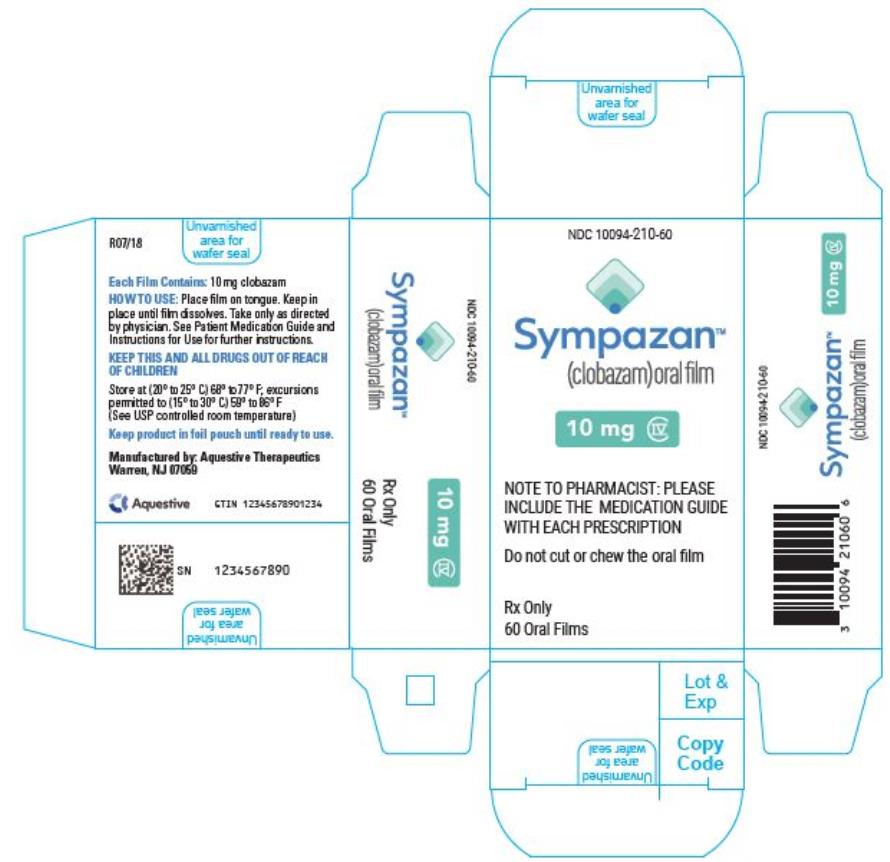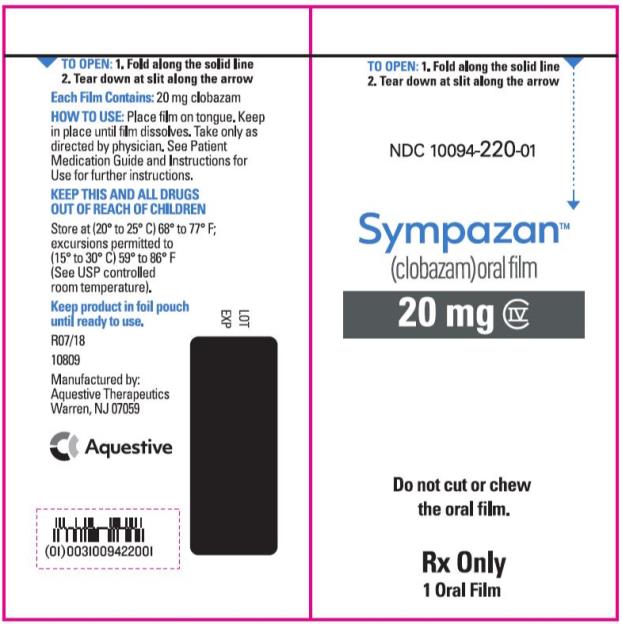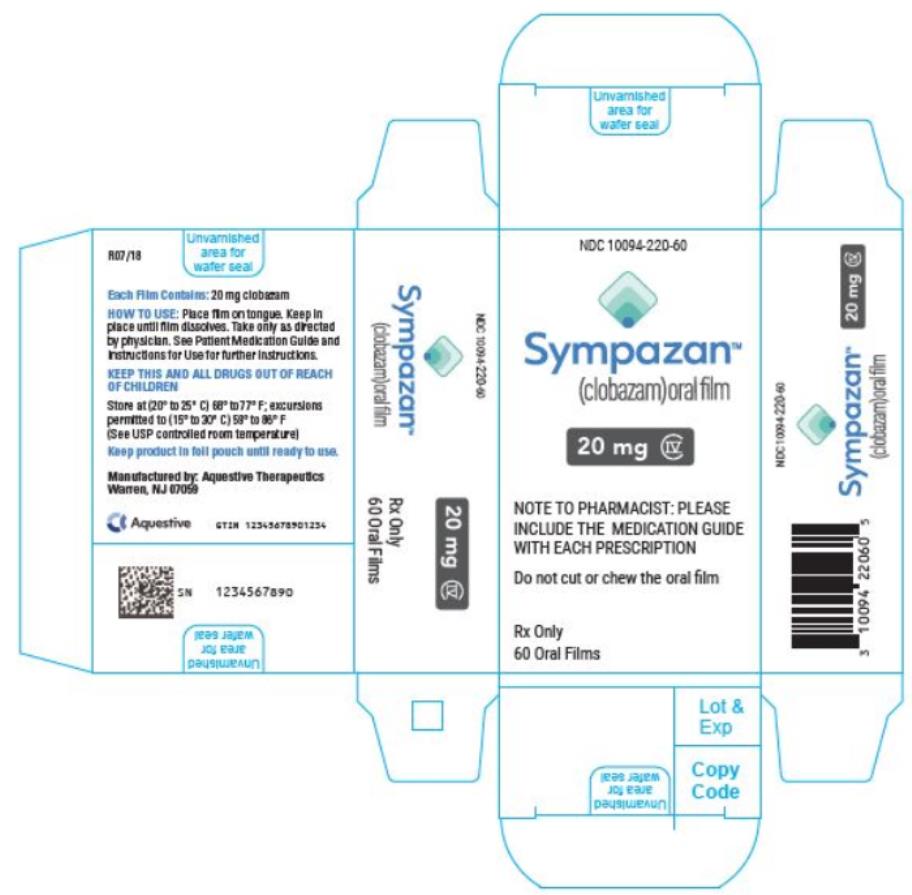 DRUG LABEL: SYMPAZAN
NDC: 10094-205 | Form: FILM
Manufacturer: Aquestive Therapeutics
Category: prescription | Type: HUMAN PRESCRIPTION DRUG LABEL
Date: 20251201
DEA Schedule: CIV

ACTIVE INGREDIENTS: CLOBAZAM 5 mg/1 1
INACTIVE INGREDIENTS: CITRIC ACID MONOHYDRATE; GLYCERYL MONOOLEATE; HYPROMELLOSES; MALTITOL; POLYETHYLENE OXIDE 200000; WATER; SODIUM PHOSPHATE, DIBASIC, ANHYDROUS; SUCRALOSE

HIGHLIGHTS OF PRESCRIBING INFORMATION

These highlights do not include all the information needed to use SYMPAZAN® safely and effectively. See full prescribing information for SYMPAZAN®.
SYMPAZAN® (clobazam) oral film, CIV
Initial U.S. Approval: 2011

RECENT MAJOR CHANGES

Warning and Precautions (5.7, 5.9) 3/2024

WARNING: RISKS FROM CONCOMITANT USE WITH OPIOIDS; ABUSE, MISUSE, AND ADDICTION; and DEPENDENCE AND WITHDRAWAL REACTIONS

See full prescribing information for complete boxed warning

- Concomitant use of benzodiazepines and opioids may result in profound sedation, respiratory depression, coma, and death. Reserve concomitant prescribing of these drugs in patients for whom alternative treatment options are inadequate. Limit dosages and durations to the minimum required. Follow patients for signs and symptoms of respiratory depression and sedation (5.1, 7.1).
- The use of benzodiazepines, including SYMPAZAN, exposes users to risks of abuse, misuse, and addiction, which can lead to overdose or death. Before prescribing SYMPAZAN and throughout treatment, assess each patient’s risk for abuse, misuse, and addiction (5.2).
- Abrupt discontinuation or rapid dosage reduction of SYMPAZAN after continued use may precipitate acute withdrawal reactions, which can be life-threatening. To reduce the risk of withdrawal reactions, use a gradual taper to discontinue SYMPAZAN (2.2, 5.3).

1 INDICATIONS AND USAGE

SYMPAZAN® is a benzodiazepine indicated for adjunctive treatment of seizures associated with Lennox-Gastaut Syndrome (LGS) in patients 2 years of age or older (1).

2 DOSAGE AND ADMINISTRATION

- For doses above 5 mg/day, administer in two divided doses (2.1)
- Patients weighing 30 kg or less: Initiate at 5 mg daily, and titrate as tolerated up to 20 mg daily (2.1)
- Patients weighing greater than 30 kg: Initiate at 10 mg daily, and titrate as tolerated up to 40 mg daily (2.1)
- Dosage adjustment is needed in following groups:
  ○ Geriatric patients (2.4, 8.5)
  ○ Known CYP2C19 poor metabolizers (2.5)
  ○ Mild or moderate hepatic impairment; no information for severe hepatic impairment (2.6, 8.8)
- Can be taken with or without food (2.3)
- Do not administer with liquids (2.3)

3 DOSAGE FORMS AND STRENGTHS

Oral Film: 5 mg, 10 mg and 20 mg (3)

4 CONTRAINDICATIONS

History of hypersensitivity to the drug or its ingredients (4)

5 WARNINGS AND PRECAUTIONS

- Somnolence or Sedation: Monitor for central nervous system (CNS) depression. Risk may be increased with concomitant use of other CNS depressants (5.4, 5.5)
- Serious Dermatological Reactions (including Stevens-Johnson Syndrome and toxic epidermal necrolysis): Discontinue SYMPAZAN® at first sign of rash unless the rash is clearly not drug-related (5.6)
- Drug Reaction with Eosinophilia and Systemic Symptoms (Dress)/Multiorgan Hypersensitivity: Discontinue if no alternative etiology (5.7)
- Suicidal Behavior and Ideation: Monitor for suicidal thoughts or behaviors (5.8)
- Neonatal Sedation and Withdrawal Syndrome: SYMPAZAN use during pregnancy can result in neonatal sedation and/or neonatal withdrawal (5.9, 8.1)

6 ADVERSE REACTIONS

Adverse reactions that occurred at least 10% more frequently than placebo in any clobazam dose included constipation, somnolence or sedation, pyrexia, lethargy, and drooling (6.1)

To report SUSPECTED ADVERSE REACTIONS, contact 1-800-518-1084 or FDA at 1-800-FDA-1088 or www.fda.gov/medwatch.

7 DRUG INTERACTIONS

- Alcohol: Increases blood levels of clobazam by about 50% (7.2)
- Drugs metabolized by CYP2D6: Lower doses of these drugs may be required when used concomitantly with SYMPAZAN® (7.3)
- Strong or Moderate CYP2C19 Inhibitors: Dosage adjustment of SYMPAZAN® may be necessary (7.4)
- Cannabidiol: May increase risk of SYMPAZAN-related adverse reactions; consider dosage adjustment if this occurs (7.4)

8 USE IN SPECIFIC POPULATIONS

- Pregnancy: Based on animal data, may cause fetal harm (8.1)

FULL PRESCRIBING INFORMATION

WARNING: RISKS FROM CONCOMITANT USE WITH OPIOIDS; ABUSE, MISUSE, AND ADDICTION; and DEPENDENCE AND WITHDRAWAL REACTIONS

- Concomitant use of benzodiazepines and opioids may result in profound sedation, respiratory depression, coma, and death. Reserve concomitant prescribing of these drugs in patients for whom alternative treatment options are inadequate. Limit dosages and durations to the minimum required. Follow patients for signs and symptoms of respiratory depression and sedation [see Warnings and Precautions (5.1), and Drug Interactions (7.1)].
- The use of benzodiazepines, including SYMPAZAN, exposes users to risks of abuse, misuse, and addiction, which can lead to overdose or death. Abuse and misuse of benzodiazepines commonly involve concomitant use of other medications, alcohol, and/or illicit substances, which is associated with an increased frequency of serious adverse outcomes. Before prescribing SYMPAZAN and throughout treatment, assess each patient’s risk for abuse, misuse, and addiction [see Warnings and Precautions (5.2)].
- The continued use of benzodiazepines, including SYMPAZAN, may lead to clinically significant physical dependence. The risks of dependence and withdrawal increase with longer treatment duration and higher daily dose. Abrupt discontinuation or rapid dosage reduction of SYMPAZAN after continued use may precipitate acute withdrawal reactions, which can be life-threatening. To reduce the risk of withdrawal reactions, use a gradual taper to discontinue SYMPAZAN or reduce the dosage [see Dosage and Administration (2.2) and Warnings and Precautions (5.3)].

1 INDICATIONS AND USAGE

SYMPAZAN® is indicated for the adjunctive treatment of seizures associated with Lennox-Gastaut Syndrome (LGS) in patients 2 years of age or older.

2 DOSAGE AND ADMINISTRATION

2.1 Dosing Information

A daily dose of SYMPAZAN® greater than 5 mg should be administered in divided doses twice daily; a 5 mg daily dose can be administered as a single dose. Dose patients according to body weight. Individualize dosing within each body weight group, based on clinical efficacy and tolerability. Each dose in Table 1 (e.g., 5 to 20 mg in 30 kg or less weight group) has been shown to be effective, although effectiveness increases with increasing dose [see Clinical Studies (14)]. Do not proceed with dose escalation more rapidly than weekly, because serum concentrations of clobazam and its active metabolite require 5 and 9 days, respectively, to reach steady-state.

Table 1: Recommended Total Daily Dosing by Weight Group
 | 30 kg or Less Body Weight | Greater than 30 kg Body Weight
Starting Dose | 5 mg | 10 mg
Starting Day 7 | 10 mg | 20 mg
Starting Day 14 | 20 mg | 40 mg

2.2 Discontinuation or Dosage Reduction of SYMPAZAN

To reduce the risk of withdrawal reactions, increased seizure frequency, and status epilepticus, use a gradual taper to discontinue SYMPAZAN or reduce the dosage. Taper by decreasing the total daily dosage by 5-10 mg/day on a weekly basis until discontinued. If a patient develops withdrawal reactions, consider pausing the taper or increasing the dosage to the previous tapered dosage level. Subsequently decrease the dosage more slowly [see Warnings and Precautions (5.3) and Drug Abuse and Dependence (9.3)].

2.3 Important Administration Instructions

Instruct patients and/or caregivers to read the “Instructions for Use” carefully for complete directions on how to properly dose and administer SYMPAZAN® oral films.

Apply SYMPAZAN® on top of the tongue where it adheres and dissolves.

SYMPAZAN® oral film can be taken with or without food [see Clinical Pharmacology (12.3)]. Do not administer with liquids. As the film dissolves, saliva should be swallowed in a normal manner, but the patient should refrain from chewing, spitting or talking.

Only one oral film should be taken at a time; if a second film is needed to complete the dosage, it should not be taken until the first film has completely dissolved.

2.4 Dosage Adjustments in Geriatric Patients

Plasma concentrations at any given dose are generally higher in geriatric patients [see Clinical Pharmacology (12.3)]. Therefore, the starting dosage should generally be 5 mg/day for all geriatric patients. Then proceed slowly with dose escalation; titrate according to weight, but to half the dosage presented in Table 1, as tolerated. If necessary and based upon clinical response, an additional titration to the maximum dosage (20 mg/day or 40 mg/day, depending on weight) may be started on day 21 [see Use in Specific Populations (8.5)].

2.5 Dosage Adjustments in CYP2C19 Poor Metabolizers

In CYP2C19 poor metabolizers, levels of N-desmethylclobazam, clobazam's active metabolite, will be increased [see Clinical Pharmacology (12.5)]. Therefore, the starting dosage should be 5 mg/day in patients known to be CYP2C19 poor metabolizers. Then proceed slowly with dose escalation; titrate according to weight, but to half the dosage presented in Table 1, as tolerated. If necessary and based upon clinical response, an additional titration to the maximum dosage (20 mg/day or 40 mg/day, depending on weight) may be started on day 21 [see Use in Specific Populations (8.6)].

2.6 Dosage Adjustments in Patients with Hepatic Impairment

SYMPAZAN® is hepatically metabolized; however, there are limited data to characterize the effect of hepatic impairment on the pharmacokinetics of SYMPAZAN®. For patients with mild to moderate hepatic impairment (Child-Pugh score 5-9), the starting dosage should be 5 mg/day (regardless of weight). Then proceed slowly with dosing escalations; titrate patients according to weight, but to half the dosage presented in Table 1, as tolerated. If necessary and based upon clinical response, an additional titration to the maximum dosage (20 mg/day or 40 mg/day, depending on weight) may be started on day 21. There is inadequate information about metabolism of clobazam in patients with severe hepatic impairment. Therefore, no dosing recommendation can be given for those patients [see Use in Specific Populations (8.8), Clinical Pharmacology (12 .3)].

3 DOSAGE FORMS AND STRENGTHS

SYMPAZAN® Oral Film: Thin, white, rectangular, orally dissolving film strips:

- 5 mg imprinted with C5
- 10 mg imprinted with C10
- 20 mg imprinted with C20

4 CONTRAINDICATIONS

SYMPAZAN® is contraindicated in patients with a history of hypersensitivity to the drug or its ingredients. Hypersensitivity reactions have included serious dermatological reactions [see Warnings and Precautions (5.6)].

5 WARNINGS AND PRECAUTIONS

5.1 Risks from Concomitant Use with Opioids

Concomitant use of benzodiazepines, including SYMPAZAN®, and opioids may result in profound sedation, respiratory depression, coma, and death. Because of these risks, reserve concomitant prescribing of benzodiazepines and opioids in patients for whom alternative treatment options are inadequate.

Observational studies have demonstrated that concomitant use of opioid analgesics and benzodiazepines increases the risk of drug-related mortality compared to use of opioids alone. If a decision is made to prescribe SYMPAZAN® concomitantly with opioids, prescribe the lowest effective dosages and minimum durations of concomitant use, and follow patients closely for signs and symptoms of respiratory depression and sedation. Advise both patients and caregivers about the risks of respiratory depression and sedation when SYMPAZAN® is used with opioids [see Drug Interactions (7.1)].

5.2 Abuse, Misuse, and Addiction

The use of benzodiazepines, including SYMPAZAN, exposes users to the risks of abuse, misuse, and addiction, which can lead to overdose or death. Abuse and misuse of benzodiazepines often (but not always) involve the use of doses greater than the maximum recommended dosage and commonly involve concomitant use of other medications, alcohol, and/or illicit substances, which is associated with an increased frequency of serious adverse outcomes, including respiratory depression, overdose, or death [see Drug Abuse and Dependence (9.2)].

Before prescribing SYMPAZAN and throughout treatment, assess each patient’s risk for abuse, misuse, and addiction (e.g., using a standardized screening tool). Use of SYMPAZAN, particularly in patients at elevated risk, necessitates counseling about the risks and proper use of SYMPAZAN along with monitoring for signs and symptoms of abuse, misuse, and addiction. Prescribe the lowest effective dosage; avoid or minimize concomitant use of CNS depressants and other substances associated with abuse, misuse, and addiction (e.g., opioid analgesics, stimulants); and advise patients on the proper disposal of unused drug. If a substance use disorder is suspected, evaluate the patient and institute (or refer them for) early treatment, as appropriate.

5.3 Dependence and Withdrawal Reactions

To reduce the risk of withdrawal reactions, use a gradual taper to discontinue SYMPAZAN or reduce the dosage [see Dosage and Administration (2.2)].

Patients at an increased risk of withdrawal adverse reactions after benzodiazepine discontinuation or rapid dosage reduction include those who take higher dosages, and those who have had longer durations of use.

Acute Withdrawal Reactions
The continued use of benzodiazepines, including SYMPAZAN, may lead to clinically significant physical dependence. Abrupt discontinuation or rapid dosage reduction of SYMPAZAN after continued use, or administration of flumazenil (a benzodiazepine antagonist) may precipitate acute withdrawal reactions, which can be life-threatening (e.g., seizures) [see Drug Abuse and Dependence (9.3)].

Protracted Withdrawal Syndrome
In some cases, benzodiazepine users have developed a protracted withdrawal syndrome with withdrawal symptoms lasting weeks to more than 12 months [see Drug Abuse and Dependence (9.3)].

5.4 Potentiation of Sedation from Concomitant Use with Central Nervous System Depressants

Since SYMPAZAN® has a central nervous system (CNS) depressant effect, patients or their caregivers should be cautioned against simultaneous use with other CNS depressant drugs or alcohol, and cautioned that the effects of other CNS depressant drugs or alcohol may be potentiated [see Drug Interactions (7.2)].

5.5 Somnolence or Sedation

SYMPAZAN® causes somnolence and sedation. In clinical trials, somnolence or sedation was reported at all effective doses and was dose-related [see Adverse Reactions (6.1)].

In general, somnolence and sedation begin within the first month of treatment and may diminish with continued treatment. Prescribers should monitor patients for somnolence and sedation, particularly with concomitant use of other central nervous system depressants. Prescribers should caution patients against engaging in hazardous activities requiring mental alertness, such as operating dangerous machinery or motor vehicles, until the effect of SYMPAZAN® is known.

5.6 Serious Dermatological Reactions

Serious skin reactions, including Stevens-Johnson Syndrome (SJS) and toxic epidermal necrolysis (TEN), have been reported with clobazam in both children and adults during the post-marketing period. Patients should be closely monitored for signs or symptoms of SJS/TEN, especially during the first 8 weeks of treatment initiation or when re-introducing therapy. SYMPAZAN® should be discontinued at the first sign of rash, unless the rash is clearly not drug-related. If signs or symptoms suggest SJS/TEN, use of this drug should not be resumed and alternative therapy should be considered [see Contraindications (4)].

5.7 Drug Reaction with Eosinophilia and Systemic Symptoms (DRESS)/Multiorgan Hypersensitivity

Drug Reaction with Eosinophilia and Systemic Symptoms (DRESS), also known as multiorgan hypersensitivity, has been reported in patients taking antiepileptic drugs, including clobazam. These events can be fatal or life-threatening, particularly if diagnosis and treatment do not occur as early as possible. DRESS typically, although not exclusively, presents with fever, rash, lymphadenopathy, and/or facial swelling, in association with other organ system involvement, such as hepatitis, nephritis, hematological abnormalities, myocarditis, or myositis, sometimes resembling an acute viral infection. Eosinophilia is often present. Because this disorder is variable in its expression, other organ systems not noted here may be involved. It is important to note that early manifestations of hypersensitivity, such as fever or lymphadenopathy, may be present even though rash is not evident. If such signs or symptoms are present, the patient should be evaluated immediately. SYMPAZAN should be discontinued if an alternative etiology for the signs or symptoms cannot be established [see Contraindications (4)].

5.8 Suicidal Behavior and Ideation

Antiepileptic drugs (AEDs), including SYMPAZAN®, increase the risk of suicidal thoughts or behavior in patients taking these drugs for any indication. Patients treated with any AED for any indication should be monitored for the emergence or worsening of depression, suicidal thoughts or behavior, and/or any unusual changes in mood or behavior.

Pooled analyses of 199 placebo-controlled clinical trials (mono- and adjunctive therapy) of 11 different AEDs showed that patients randomized to one of the AEDs had approximately twice the risk (adjusted relative risk 1.8, 95% confidence interval [CI]: 1.2, 2.7) of suicidal thinking or behavior compared to patients randomized to placebo. In these trials, which had a median treatment duration of 12 weeks, the estimated incidence rate of suicidal behavior or ideation among 27,863 AED-treated patients was 0.43%, compared to 0.24% among 16,029 placebo-treated patients, representing an increase of approximately one case of suicidal thinking or behavior for every 530 patients treated. There were four suicides in drug-treated patients in the trials and none in placebo-treated patients, but the number is too small to allow any conclusion about drug effect on suicide.

The increased risk of suicidal thoughts or behavior with AEDs was observed as early as one week after starting drug treatment with AEDs and persisted for the duration of treatment assessed. Because most trials included in the analysis did not extend beyond 24 weeks, the risk of suicidal thoughts or behavior beyond 24 weeks could not be assessed.

The risk of suicidal thoughts or behavior was generally consistent among drugs in the data analyzed. The finding of increased risk with AEDs of varying mechanisms of action and across a range of indications suggests that the risk applies to all AEDs used for any indication. The risk did not vary substantially by age (5-100 years) in the clinical trials analyzed. Table 2 shows absolute and relative risk by indication for all evaluated AEDs.

Table 2: Risk by Indication for Antiepileptic Drugs in the Pooled Analysis
Indication | Placebo Patients with Events per 1000 Patients | Drug Patients with Events per 1000 Patients | Relative Risk: Incidence of Drug Events in Drug Patients/Incidence in Placebo Patients | Risk Difference: Additional Drug Patients with Events per 1000 Patients
Epilepsy | 1.0 | 3.4 | 3.5 | 2.4
Psychiatric | 5.7 | 8.5 | 1.5 | 2.9
Other | 1.0 | 1.8 | 1.9 | 0.9
Total | 2.4 | 4.3 | 1.8 | 1.9

The relative risk for suicidal thoughts or behavior was higher in clinical trials for epilepsy than in clinical trials for psychiatric or other conditions, but the absolute risk differences were similar for the epilepsy and psychiatric indications.

Anyone considering prescribing SYMPAZAN® or any other AED must balance the risk of suicidal thoughts or behavior with the risk of untreated illness. Epilepsy and many other illnesses for which AEDs are prescribed are themselves associated with morbidity and mortality and an increased risk of suicidal thoughts and behavior. Should suicidal thoughts and behavior emerge during treatment, the prescriber needs to consider whether the emergence of these symptoms in any given patient may be related to the illness being treated.

5.9 Neonatal Sedation and Withdrawal Syndrome

Use of SYMPAZAN late in pregnancy can result in sedation (respiratory depression, lethargy, hypotonia) and/or withdrawal symptoms (hyperreflexia, irritability, restlessness, tremors, inconsolable crying, and feeding difficulties) in the neonate [see Use in Specific Populations (8.1)]. Monitor neonates exposed to SYMPAZAN during pregnancy or labor for signs of sedation and monitor neonates exposed to SYMPAZAN during pregnancy for signs of withdrawal; manage these neonates accordingly.

6 ADVERSE REACTIONS

Clinically significant adverse reactions that appear in other sections of the labeling include the following:

- Risks from Concomitant Use with Opioids [see Warnings and Precautions (5.1)]
- Abuse, Misuse, and Addiction [see Warnings and Precautions (5.2)]
- Dependence and Withdrawal Reactions [see Warnings and Precautions (5.3)]
- Potentiation of Sedation from Concomitant Use with Central Nervous System Depressants [see Warnings and Precautions (5.4)]
- Somnolence or Sedation [see Warnings and Precautions (5.5)]
- Serious Dermatological Reactions [see Contraindications (4), Warnings and Precautions (5.6)]
- Drug Reaction with Eosinophilia and Systemic Symptoms (DRESS)/Multiorgan Hypersensitivity [see Warnings and Precautions (5.7)]
- Suicidal Behavior and Ideation [see Warnings and Precautions (5.8)]
- Neonatal Sedation and Withdrawal Syndrome [see Warnings and Precautions (5.9)]

6.1 Clinical Trials Experience

Because clinical trials are conducted under widely varying conditions, adverse reaction rates observed in the clinical trials of a drug cannot be directly compared to rates in the clinical trials of another drug and may not reflect the rates observed in practice. The following adverse events have been reported in clinical trials of patients treated with clobazam, the active ingredient of SYMPAZAN®.

During its development for the adjunctive treatment of seizures associated with LGS, clobazam was administered to 333 healthy volunteers and 300 patients with a current or prior diagnosis of LGS, including 197 patients treated for 12 months or more. The conditions and duration of exposure varied greatly and included single- and multiple-dose clinical pharmacology studies in healthy volunteers and two double-blind studies in patients with LGS (Study 1 and 2) [see Clinical Studies (14)]. Only Study 1 included a placebo group, allowing comparison of adverse reaction rates on clobazam at several doses to placebo.

Adverse Reactions Leading to Discontinuation in an LGS Placebo Controlled Clinical Trial (Study 1)
The adverse reactions associated with clobazam treatment discontinuation in ≥1% of patients in decreasing order of frequency included lethargy, somnolence, ataxia, aggression, fatigue, and insomnia.

Most Common Adverse Reactions in an LGS Placebo Controlled Clinical Trial (Study 1)
Table 3 lists the adverse reactions that occurred in ≥5% of clobazam-treated patients (at any dose), and at a rate greater than placebo-treated patients, in the randomized, double-blind, placebo-controlled, parallel group clinical study of adjunctive AED therapy for 15 weeks (Study 1).

Table 3: Adverse Reactions Reported for ≥5% of Patients and More Frequently than Placebo in Any Treatment Group
 |  |  | Clobazam Dose Level |  |  |  | All Clobazam N=179 %
 |  | Placebo N=59 % | Lowa N=58 % | Mediumb N=62 % |  | Highc N=59 %
Gastrointestinal Disorders
Vomiting |  | 5 | 9 | 5 |  | 7 | 7
Constipation |  | 0 | 2 | 2 |  | 10 | 5
Dysphagia |  | 0 | 0 | 0 |  | 5 | 2
General Disorders and Administration Site Conditions
Pyrexia |  | 3 | 17 | 10 | 12 |  | 13
Irritability |  | 5 | 3 | 11 | 5 |  | 7
Fatigue |  | 2 | 5 | 5 | 3 |  | 5
Infections and Infestations
Upper respiratory tract infection |  | 10 | 10 | 13 | 14 |  | 12
Pneumonia |  | 2 | 3 | 3 | 7 |  | 4
Urinary tract infection |  | 0 | 2 | 5 | 5 |  | 4
Bronchitis |  | 0 | 2 | 0 | 5 |  | 2
Metabolism and Nutrition Disorders
Decreased appetite | 3 |  | 3 | 0 | 7 |  | 3
Increased appetite | 0 |  | 2 | 3 | 5 |  | 3
Nervous System Disorders
Somnolence or Sedation | 15 |  | 17 | 27 | 32 |  | 26
Somnolence | 12 |  | 16 | 24 | 25 |  | 22
Sedation | 3 |  | 2 | 3 | 9 |  | 5
Lethargy | 5 |  | 10 | 5 | 15 |  | 10
Drooling | 3 |  | 0 | 13 | 14 |  | 9
Ataxia | 3 |  | 3 | 2 | 10 |  | 5
Psychomotor hyperactivity | 3 |  | 3 | 3 | 5 |  | 4
Dysarthria | 0 |  | 2 | 2 | 5 |  | 3
Psychiatric Disorders
Aggression | 5 |  | 3 | 8 | 14 |  | 8
Insomnia | 2 |  | 2 | 5 | 7 |  | 5
Respiratory Disorders
Cough | 0 |  | 3 | 5 | 7 |  | 5

a Maximum daily dose of 5 mg for ≤30 kg body weight; 10 mg for >30 kg body weight
b Maximum daily dose of 10 mg for ≤30 kg body weight; 20 mg for >30 kg body weight
c Maximum daily dose of 20 mg for ≤30 kg body weight; 40 mg for >30 kg body weight

6.2 Postmarketing Experience

The following adverse reactions have been identified during post-approval use of clobazam tablets. These reactions are reported voluntarily from a population of uncertain size; therefore, it is not possible to estimate their frequency or establish a causal relationship to drug exposure. Adverse reactions are categorized by system organ class.

Blood Disorders: Anemia, eosinophilia, leukopenia, thrombocytopenia
Eye Disorders: Diplopia, vision blurred
Gastrointestinal Disorders: Abdominal distention
General Disorders and Administration Site Conditions: Hypothermia
Investigations: Hepatic enzyme increased
Musculoskeletal: Muscle spasms
Psychiatric Disorders: Agitation, anxiety, apathy, confusional state, depression, delirium, delusion, hallucination
Renal and Urinary Disorders: Urinary retention
Respiratory Disorders: Aspiration, respiratory depression
Skin and Subcutaneous Tissue Disorders: Rash, urticaria, angioedema, and facial and lip edema

7 DRUG INTERACTIONS

7.1 Opioids

The concomitant use of benzodiazepines and opioids increases the risk of respiratory depression because of actions at different receptor sites in the CNS that control respiration. Benzodiazepines interact at GABAA sites, and opioids interact primarily at mu receptors. When benzodiazepines and opioids are combined, the potential for benzodiazepines to significantly worsen opioid-related respiratory depression exists. Limit dosage and duration of concomitant use of benzodiazepines and opioids, and follow patients closely for respiratory depression and sedation [see Warnings and Precautions (5.1)].

7.2 CNS Depressants and Alcohol

Concomitant use of SYMPAZAN® with other CNS depressants may increase the risk of sedation and somnolence [see Warnings and Precautions (5.4)].

Alcohol, as a CNS depressant, will interact with SYMPAZAN® in a similar way and also increases clobazam's maximum plasma exposure by approximately 50%. Therefore, caution patients or their caregivers against simultaneous use with other CNS depressant drugs or alcohol, and caution that the effects of other CNS depressant drugs or alcohol may be potentiated [see Warnings and Precautions (5.4)].

7.3 Effect of SYMPAZAN® on Other Drugs

Hormonal Contraceptives

SYMPAZAN® is a weak CYP3A4 inducer. As some hormonal contraceptives are metabolized by CYP3A4, their effectiveness may be diminished when given with SYMPAZAN®. Additional non-hormonal forms of contraception are recommended when using SYMPAZAN® [see Clinical Pharmacology (12.3), Patient Counseling Information (17)].

Drugs Metabolized by CYP2D6

SYMPAZAN® inhibits CYP2D6. Dose adjustment of drugs metabolized by CYP2D6 may be necessary [see Clinical Pharmacology (12.3)].

7.4 Effect of Other Drugs on SYMPAZAN®

Strong and Moderate Inhibitors of CYP2C19
Coadministration with strong or moderate inhibitors of CYP2C19 may result in increased exposure to N-desmethylclobazam, the active metabolite of clobazam. This may increase the risk of dose-related adverse reactions. Dosage adjustment of SYMPAZAN® may be necessary when co-administered with strong CYP2C19 inhibitors (e.g., fluconazole, fluvoxamine, ticlopidine) or moderate CYP2C19 inhibitors (e.g., omeprazole) [see Clinical Pharmacology (12.3)].

Effect of Cannabidiol on SYMPAZAN®

Coadministration of cannabidiol, a CYP3A4 and CYP2C19 substrate and a CYP2C19 inhibitor, with clobazam may increase the risk of clobazam-related adverse reactions [see Warnings and Precautions (5.4, 5.5), Clinical Pharmacology (12.3)]. Consider a reduction in dosage of cannabidiol or clobazam if adverse reactions known to occur with SYMPAZAN are experienced.

8 USE IN SPECIFIC POPULATIONS

8.1 Pregnancy

Pregnancy Exposure Registry

There is a pregnancy exposure registry that monitors pregnancy outcomes in women exposed to AEDs, such as SYMPAZAN®, during pregnancy. Healthcare providers are encouraged to recommend that pregnant women taking SYMPAZAN® enroll in the North American Antiepileptic Drug (NAAED) Pregnancy Registry by calling 1-888-233-2334 or online at http://www.aedpregnancyregistry.org/

Risk Summary

Neonates born to mothers using benzodiazepines late in pregnancy have been reported to experience symptoms of sedation and/or neonatal withdrawal [see Warnings and Precautions (5.9) and Clinical Considerations]. Available data from published observational studies of pregnant women exposed to benzodiazepines do not report a clear association with benzodiazepines and major birth defects (see Data). Administration of clobazam to pregnant rats and rabbits during the period of organogenesis or to rats throughout pregnancy and lactation resulted in developmental toxicity, including increased incidences of fetal malformations and mortality, at plasma exposures for clobazam and its major active metabolite, N-desmethylclobazam, below those expected at therapeutic doses in patients [see Animal Data].

Data for other benzodiazepines suggest the possibility of long-term effects on neurobehavioral and immunological function in animals following prenatal exposure to benzodiazepines at clinically relevant doses.

The background risk of major birth defects and miscarriage for the indicated population is unknown. All pregnancies have a background risk of birth defect, loss, or other adverse outcomes. In the U.S. general population, the estimated background risk of major birth defects and miscarriage in clinically recognized pregnancies is 2%-4% and 15% -20%, respectively.

Clinical Considerations

Fetal/Neonatal Adverse Reactions

Benzodiazepines cross the placenta and may produce respiratory depression, hypotonia, and sedation in neonates. Monitor neonates exposed to SYMPAZAN during pregnancy or labor for signs of sedation, respiratory depression, hypotonia, and feeding problems. Monitor neonates exposed to SYMPAZAN during pregnancy for signs of withdrawal. Manage these neonates accordingly [see Warnings and Precautions (5.9)].

Data

Human Data

Published data from observational studies on the use of benzodiazepines during pregnancy do not report a clear association with benzodiazepines and major birth defects. Although early studies reported an increased risk of congenital malformations with diazepam and chlordiazepoxide, there was no consistent pattern noted. In addition, the majority of more recent case-control and cohort studies of benzodiazepine use during pregnancy, which were adjusted for confounding exposures to alcohol, tobacco and other medications, have not confirmed these findings.

Animal Data

In a study in which clobazam (0, 150, 450, or 750 mg/kg/day) was orally administered to pregnant rats throughout the period of organogenesis, embryofetal mortality and incidences of fetal skeletal variations were increased at all doses. The low-effect dose for embryofetal developmental toxicity in rats (150 mg/kg/day) was associated with plasma exposures (AUC) for clobazam and its major active metabolite, N-desmethylclobazam, lower than those in humans at the maximum recommended human dose (MRHD) of 40 mg/day.

Oral administration of clobazam (0, 10, 30, or 75 mg/kg/day) to pregnant rabbits throughout the period of organogenesis resulted in decreased fetal body weights, and increased incidences of fetal malformations (visceral and skeletal) at the mid and high doses, and an increase in embryofetal mortality at the high dose. Incidences of fetal variations were increased at all doses. The highest dose tested was associated with maternal toxicity (ataxia and decreased activity). The low effect dose for embryofetal developmental toxicity in rabbits (10 mg/kg/day) was associated with plasma exposures for clobazam and N-desmethylclobazam lower than those in humans at the MRHD.

Oral administration of clobazam (0, 50, 350, or 750 mg/kg/day) to rats throughout pregnancy and lactation resulted in increased embryofetal mortality at the high dose, decreased pup survival at the mid and high doses and alterations in offspring behavior (locomotor activity) at all doses. The low-effect dose for adverse effects on preand postnatal development in rats (50 mg/kg/day) was associated with plasma exposures for clobazam and N-desmethylclobazam lower than those in humans at the MRHD.

8.2 Lactation

Risk Summary

SYMPAZAN® is excreted in human milk (see Data). There are reports of sedation, poor feeding and poor weight gain in infants exposed to benzodiazepines through breast milk. There are no data on the effects of clobazam on milk production.

The developmental and health benefits of breastfeeding should be considered along with the mother’s clinical need for SYMPAZAN® and any potential adverse effects on the breastfed infant from SYMPAZAN® or from the underlying maternal condition.

Clinical Considerations

Adverse reactions such as somnolence and difficulty feeding have been reported in infants during breastfeeding in postmarketing experience with clobazam. Infants exposed to SYMPAZAN through breast milk should be monitored for sedation, poor feeding and poor weight gain.

Data

Scientific literature on clobazam use during lactation is limited. After short-term administration, clobazam and N-desmethylclobazam are transferred into breast milk.

8.3 Females and Males of Reproductive Potential

Administration of clobazam to rats prior to and during mating and early gestation resulted in adverse effects on fertility and early embryonic development at plasma exposures for clobazam and its major active metabolite, N-desmethylclobazam, below those in humans at the MRHD [see Nonclinical Toxicology (13.1)].

8.4 Pediatric Use

Safety and effectiveness for the adjunctive treatment of seizures associated with Lennox-Gastaut syndrome in pediatric patients 2 years of age and older have been established in two adequate and well-controlled studies [see Clinical Studies (14)].

Safety and effectiveness in patients less than 2 years of age have not been established.

Juvenile Animal Data

In a study in which clobazam (0, 4, 36, or 120 mg/kg/day) was orally administered to rats during the juvenile period of development (postnatal days 14 to 48), adverse effects on growth (decreased bone density and bone length) and behavior (altered motor activity and auditory startle response; learning deficit) were observed at the high dose. The effect on bone density, but not on behavior, was reversible when drug was discontinued. The no-effect level for juvenile toxicity (36 mg/kg/day) was associated with plasma exposures (AUC) to clobazam and its major active metabolite, N-desmethylclobazam, less than those expected at therapeutic doses in pediatric patients.

8.5 Geriatric Use

Clinical studies of clobazam did not include sufficient numbers of subjects aged 65 and over to determine whether they respond differently from younger subjects. However, elderly subjects appear to eliminate clobazam more slowly than younger subjects based on population pharmacokinetic analysis. For these reasons, dosage modification is recommended [see Dosage and Administration (2.4), Clinical Pharmacology (12.3)].

8.6 CYP2C19 Poor Metabolizers

Concentrations of clobazam's active metabolite, N-desmethylclobazam, are higher in CYP2C19 poor metabolizers than in extensive metabolizers. For this reason, dosage modification is recommended [see Dosage and Administration (2.5), Clinical Pharmacology (12.3)].

8.7 Renal Impairment

The pharmacokinetics of clobazam were evaluated in patients with mild and moderate renal impairment. There were no significant differences in systemic exposure (AUC and Cmax) between patients with mild or moderate renal impairment and healthy subjects. No dose adjustment is required for patients with mild and moderate renal impairment. There is essentially no experience with SYMPAZAN® in patients with severe renal impairment or ESRD. It is not known if clobazam or its active metabolite, N-desmethyl-clobazam, is dialyzable [see Clinical Pharmacology (12.3)].

8.8 Hepatic Impairment

SYMPAZAN® is hepatically metabolized; however, there are limited data to characterize the effect of hepatic impairment on the pharmacokinetics of clobazam. For this reason, dosage adjustment is recommended in patients with mild to moderate hepatic impairment (Child-Pugh score 5-9) [see Dosage and Administration (2.6)]. There is inadequate information about metabolism of SYMPAZAN® in patients with severe hepatic impairment [see Clinical Pharmacology (12.3)].

9 DRUG ABUSE AND DEPENDENCE

9.1 Controlled Substance

SYMPAZAN® contains clobazam, a Schedule IV controlled substance.

9.2 Abuse

SYMPAZAN is a benzodiazepine and a CNS depressant with a potential for abuse and addiction. Abuse is the intentional, non-therapeutic use of a drug, even once, for its desirable psychological or physiological effects. Misuse is the intentional use, for therapeutic purposes, of a drug by an individual in a way other than prescribed by a health care provider or for whom it was not prescribed. Drug addiction is a cluster of behavioral, cognitive, and physiological phenomena that may include a strong desire to take the drug, difficulties in controlling drug use (e.g., continuing drug use despite harmful consequences, giving a higher priority to drug use than other activities and obligations), and possible tolerance or physical dependence. Even taking benzodiazepines as prescribed may put patients at risk for abuse and misuse of their medication. Abuse and misuse of benzodiazepines may lead to addiction.

Abuse and misuse of benzodiazepines often (but not always) involve the use of doses greater than the maximum recommended dosage and commonly involve concomitant use of other medications, alcohol, and/or illicit substances, which is associated with an increased frequency of serious adverse outcomes, including respiratory depression, overdose, or death. Benzodiazepines are often sought by individuals who abuse drugs and other substances, and by individuals with addictive disorders [see Warnings and Precautions (5.2)].

The following adverse reactions have occurred with benzodiazepine abuse and/or misuse: abdominal pain, amnesia, anorexia, anxiety, aggression, ataxia, blurred vision, confusion, depression, disinhibition, disorientation, dizziness, euphoria, impaired concentration and memory, indigestion, irritability, muscle pain, slurred speech, tremors, and vertigo.

The following severe adverse reactions have occurred with benzodiazepine abuse and/or misuse: delirium, paranoia, suicidal ideation and behavior, seizures, coma, breathing difficulty, and death. Death is more often associated with polysubstance use (especially benzodiazepines with other CNS depressants such as opioids and alcohol). The World Health Organization epidemiology database contains reports of drug abuse, misuse, and overdoses associated with clobazam.

9.3 Dependence

Physical Dependence

SYMPAZAN may produce physical dependence from continued therapy. Physical dependence is a state that develops as a result of physiological adaptation in response to repeated drug use, manifested by withdrawal signs and symptoms after abrupt discontinuation or a significant dose reduction of a drug. Abrupt discontinuation or rapid dosage reduction of benzodiazepines or administration of flumazenil, a benzodiazepine antagonist, may precipitate acute withdrawal reactions, including seizures, which can be life-threatening. Patients at an increased risk of withdrawal adverse reactions after benzodiazepine discontinuation or rapid dosage reduction include those who take higher dosages (i.e., higher and/or more frequent doses) and those who have had longer durations of use [see Warnings and Precautions (5.3)].

To reduce the risk of withdrawal reactions, use a gradual taper to discontinue SYMPAZAN or reduce the dosage [see Dosage and Administration (2.2) and Warnings and Precautions (5.3)].

Acute Withdrawal Signs and Symptoms

Acute withdrawal signs and symptoms associated with benzodiazepines have included abnormal involuntary movements, anxiety, blurred vision, depersonalization, depression, derealization, dizziness, fatigue, gastrointestinal adverse reactions (e.g., nausea, vomiting, diarrhea, weight loss, decreased appetite), headache, hyperacusis, hypertension, irritability, insomnia, memory impairment, muscle pain and stiffness, panic attacks, photophobia, restlessness, tachycardia, and tremor. More severe acute withdrawal signs and symptoms, including life-threatening reactions, have included catatonia, convulsions, delirium tremens, depression, hallucinations, mania, psychosis, seizures, and suicidality.

Protracted Withdrawal Syndrome

Protracted withdrawal syndrome associated with benzodiazepines is characterized by anxiety, cognitive impairment, depression, insomnia, formication, motor symptoms (e.g., weakness, tremor, muscle twitches), paresthesia, and tinnitus that persists beyond 4 to 6 weeks after initial benzodiazepine withdrawal. Protracted withdrawal symptoms may last weeks to more than 12 months. As a result, there may be difficulty in differentiating withdrawal symptoms from potential re-emergence or continuation of symptoms for which the benzodiazepine was being used.

Tolerance

Tolerance to SYMPAZAN may develop from continued therapy. Tolerance is a physiological state characterized by a reduced response to a drug after repeated administration (i.e., a higher dose of a drug is required to produce the same effect that was once obtained at a lower dose). Tolerance to the therapeutic effect of SYMPAZAN may develop; however, little tolerance develops to the amnestic reactions and other cognitive impairments caused by benzodiazepines.

10 OVERDOSAGE

Overdosage of benzodiazepines is characterized by central nervous system depression ranging from drowsiness to coma. In mild to moderate cases, symptoms can include drowsiness, confusion, dysarthria, lethargy, hypnotic state, diminished reflexes, ataxia, and hypotonia. Rarely, paradoxical or disinhibitory reactions (including agitation, irritability, impulsivity, violent behavior, confusion, restlessness, excitement, and talkativeness) may occur. In severe overdosage cases, patients may develop respiratory depression and coma. Overdosage of benzodiazepines in combination with other CNS depressants (including alcohol and opioids) may be fatal [see Warnings and Precautions (5.2)]. Markedly abnormal (lowered or elevated) blood pressure, heart rate, or respiratory rate raise the concern that additional drugs and/or alcohol are involved in the overdosage.

In managing benzodiazepine overdosage, employ general supportive measures, including intravenous fluids and airway maintenance. Flumazenil, a specific benzodiazepine receptor antagonist indicated for the complete or partial reversal of the sedative effects of benzodiazepines in the management of benzodiazepine overdosage, can lead to withdrawal and adverse reactions, including seizures, particularly in the context of mixed overdosage with drugs that increase seizure risk (e.g., tricyclic and tetracyclic antidepressants) and in patients with long-term benzodiazepine use and physical dependency. The risk of withdrawal seizures with flumazenil use may be increased in patients with epilepsy. Flumazenil is contraindicated in patients who have received a benzodiazepine for control of a potentially life-threatening condition (e.g., status epilepticus). If the decision is made to use flumazenil, it should be used as an adjunct to, not as a substitute for, supportive management of benzodiazepine overdosage. See the flumazenil injection Prescribing Information.

Consider contacting the Poison Help line (1-800-222-1222) or a medical toxicologist for additional overdosage management recommendations.

11 DESCRIPTION

SYMPAZAN® contains clobazam, a benzodiazepine derivative, which is chemically known as 7-Chloro-1-methyl-5-phenyl-1H-1,5 benzodiazepine-2,4(3H,5H)-dione with a molecular formula of C16H13ClN2O2, molecular weight of 300.74, and it has the following structural formula:

Clobazam is a white or almost white, crystalline powder with a slightly bitter taste. It is slightly soluble in water and sparingly soluble in ethanol.

Each SYMPAZAN® Oral Film contains 5 mg, 10 mg or 20 mg of clobazam and the following inactive ingredients: artificial cooling flavor, citric acid, glycerol monooleate, hypromellose, maltitol, natural and artificial bitter masker, natural raspberry type flavor, polyethylene oxide, purified water, sodium phosphate dibasic, and sucralose.

12 CLINICAL PHARMACOLOGY

12.1 Mechanism of Action

The exact mechanism of action for clobazam, a 1,5-benzodiazepine, is not fully understood but is thought to involve potentiation of GABAergic neurotransmission resulting from binding at the benzodiazepine site of the GABAA receptor.

12.2 Pharmacodynamics

Effects on Electrocardiogram
The effect of clobazam 20 mg and 80 mg administered twice daily on QTc interval was evaluated in a randomized, evaluator-blinded, placebo-, and active-controlled (moxifloxacin 400 mg) parallel thorough QT study in 280 healthy subjects. In a study with demonstrated ability to detect small effects, the upper bound of the one-sided 95% confidence interval for the largest placebo adjusted, baseline-corrected QTc based on the Fridericia correction method was below 10 ms, the threshold for regulatory concern. Thus, at a dose two times the maximum recommended dose, clobazam did not prolong the QTc interval to any clinically relevant extent.

12.3 Pharmacokinetics

SYMPAZAN® Oral Films at single doses of 10 mg and 20 mg clobazam have been shown to be bioequivalent (Cmax and AUC) to clobazam tablets at equivalent doses. Following single-dose administration of SYMPAZAN®, peak plasma levels (Cmax) and the area under the curve (AUC) of clobazam are dose-proportional over the dose range of 10-20 mg. Based on a population pharmacokinetic analysis with clobazam tablets, the pharmacokinetics of clobazam are linear from 5-160 mg/day. Clobazam is converted to N-desmethylclobazam which has about 1/5 the activity of clobazam. The estimated mean elimination half-lives (t1/2) of clobazam and N-desmethylclobazam were 36-42 hours and 71-82 hours, respectively.

Absorption

The time to peak concentrations (Tmax) of SYMPAZAN® clobazam oral film under fasted conditions ranged from 0.33 to 4.0 hours after single-dose administration. The administration of clobazam tablets with food does not affect absorption. Although not studied, the oral bioavailability of SYMPAZAN® oral film is unlikely to be affected under fed conditions.

Distribution

Clobazam is lipophilic and distributes rapidly throughout the body. The apparent volume of distribution at steady state was approximately 100 L. The in vitro plasma protein binding of clobazam and N-desmethylclobazam is approximately 80-90% and 70%, respectively.

Metabolism and Excretion

Clobazam is extensively metabolized in the liver, with approximately 2% of the dose recovered in urine and 1% in feces as unchanged drug. The major metabolic pathway of clobazam involves N-demethylation, primarily by CYP3A4 and to a lesser extent by CYP2C19 and CYP2B6. N-desmethylclobazam, an active metabolite, is the major circulating metabolite in humans, and at therapeutic doses, plasma concentrations are 3-5 times higher than those of the parent compound. Based on animal and in vitro receptor binding data, estimates of the relative potency of N-desmethylclobazam compared to parent compound range from 1/5 to equal potency. N-desmethylclobazam is extensively metabolized, mainly by CYP2C19. N-desmethylclobazam and its metabolites comprise ~94% of the total drug-related components in urine. Following a single oral dose of radiolabeled drug, approximately 11% of the dose was excreted in the feces and approximately 82% was excreted in the urine.

The polymorphic CYP2C19 is the major contributor to the metabolism of the pharmacologically active N-desmethylclobazam [see Clinical Pharmacology (12.5)]. In CYP2C19 poor metabolizers, levels of N-desmethylclobazam were 5-fold higher in plasma and 2- to 3-fold higher in the urine than in CYP2C19 extensive metabolizers.

Pharmacokinetics in Specific Populations

Age
Population pharmacokinetic analyses showed that the clearance of clobazam is lower in elderly subjects compared to other age groups (ages less than 64). Dosing should be adjusted in the elderly [see Dosage and Administration (2.4)].

Sex
Population pharmacokinetic analyses showed no difference in the clearance of clobazam between women and men.

Race
Population pharmacokinetic analyses including Caucasian (75%), African American (15%), and Asian (9%) subjects showed that there is no evidence of clinically significant effect of race on the clearance of clobazam.

Renal Impairment
The effect of renal impairment on the pharmacokinetics of clobazam was evaluated in patients with mild (creatinine clearance [CLCR] >50 to 80 mL/min; N=6) and moderate (CLCR=30 to 50 mL/min; N=6) renal dysfunction, with matching healthy controls (N=6), following administration of multiple doses of clobazam 20 mg/day. There were insignificant changes in Cmax (3-24%) and AUC (≤13%) for clobazam or N-desmethylclobazam in patients with mild or moderate renal impairment compared to patients with normal renal function. Patients with severe renal impairment or ESRD were not included in this study.

Hepatic Impairment
There are limited data to characterize the effect of hepatic impairment on the pharmacokinetics of clobazam. In a small study, the pharmacokinetics of a 20 mg single oral dose of clobazam in 9 patients with liver impairment were compared to healthy controls (N=6). The Cmax and the mean plasma clearance of clobazam, as well as the Cmax of N-desmethylclobazam, showed no significant change compared to the healthy controls. The AUC values of N-desmethylclobazam in these patients were not available. Adjust dosage in patients with hepatic impairment [see Dosage and Administration (2.6)].

Drug Interaction Studies

In vitro studies:
Clobazam did not inhibit CYP1A2, CYP2C8, CYP2C9, CYP2C19, CYP2D6, CYP3A4, UGT1A1, UGT1A4, UGT1A6, or UGT2B4 in vitro. N-desmethylclobazam showed weak inhibition of CYP2C9, UGT1A4, UGT1A6 and UGT2B4.

Clobazam and N-desmethylclobazam did not significantly increase CYP1A2 or CYP2C19 activities, but did induce CYP3A4 activity in a concentration-dependent manner. Clobazam and N-desmethylclobazam also increased UGT1A1 mRNA but at concentrations much higher than therapeutic levels. The potential for clobazam or N-desmethylclobazam to induce CYP2B6 and CYP2C8 has not been evaluated.

Clobazam and N-desmethylclobazam do not inhibit P-glycoprotein (P-gp), but are P-gp substrates.

In vivo studies:

Potential for Clobazam to Affect Other Drugs
The effect of repeated 40 mg once-daily doses of clobazam on the pharmacokinetic profiles of single-dose dextromethorphan (CYP2D6 substrate), midazolam (CYP3A4 substrate), caffeine (CYP1A2 substrate), and tolbutamide (CYP2C9 substrate), was studied when these probe substrates were given as a drug cocktail (N=18).

Clobazam increased AUC and Cmax of dextromethorphan by 90% and 59%, respectively, reflecting its inhibition of CYP2D6 in vivo. Drugs metabolized by CYP2D6 may require dose adjustment when used with clobazam.

Clobazam decreased the AUC and Cmax of midazolam by 27% and 24%, respectively, and increased the AUC and Cmax of the metabolite 1-hydroxymidazolam by 4-fold and 2-fold, respectively. This level of induction does not call for dosage adjustment of drugs that are primarily metabolized by CYP3A4 when used concomitantly with clobazam. Some hormonal contraceptives are metabolized by CYP3A4 and their effectiveness may be diminished when given with SYMPAZAN® [see Drug Interactions (7.3)]. Repeated clobazam doses had no effect on caffeine and tolbutamide.

A population pharmacokinetic analysis indicated clobazam did not affect the exposure of valproic acid (a CYP2C9/2C19 substrate) or lamotrigine (a UGT substrate).

Potential for Other Drugs to Affect SYMPAZAN®
Co-administration of ketoconazole (a strong CYP3A4 inhibitor) 400 mg once-daily for 5 days increased clobazam AUC by 54%, with an insignificant effect on clobazam Cmax. There was no significant change in AUC and Cmax of N-desmethylclobazam (N=18).

Strong (e.g., fluconazole, fluvoxamine, ticlopidine) and moderate (e.g., omeprazole) inhibitors of CYP2C19 may result in up to a 5-fold increase in exposure to N-desmethylclobazam, the active metabolite of clobazam, based on extrapolation from pharmacogenomic data [see Clinical Pharmacology (12.5)]. Dosage adjustment of SYMPAZAN® may be necessary when co-administered with strong or moderate CYP2C19 inhibitors [see Drug Interactions (7.4)].

Coadministration of cannabidiol (a CYP3A4 and CYP2C19 substrate; an inhibitor of CYP2C19) produced a 3-fold increase in plasma concentrations of N-desmethylclobazam, the active metabolite of clobazam (a substrate of CYP2C19). This may increase the risk of clobazam-related adverse reactions [see Warnings and Precautions (5.4, 5.5), Drug Interactions (7.4)].

The effects of concomitant antiepileptic drugs that are CYP3A4 inducers (phenobarbital, phenytoin, and carbamazepine), CYP2C19 inducers (valproic acid, phenobarbital, phenytoin, and carbamazepine), and CYP2C19 inhibitors (felbamate and oxcarbazepine) were evaluated using data from clinical trials. Results of population pharmacokinetic analysis show that these concomitant antiepileptic drugs did not significantly alter the pharmacokinetics of clobazam or N-desmethylclobazam at steady-state.

Alcohol has been reported to increase the maximum plasma exposure of clobazam by approximately 50%. Alcohol may have additive CNS depressant effects when taken with SYMPAZAN® [see Warnings and Precautions (5.4), Drug Interactions (7.2)].

12.5 Pharmacogenomics

The polymorphic CYP2C19 is the main enzyme that metabolizes the pharmacologically active N-desmethyl-clobazam. Compared to CYP2C19 extensive metabolizers, N-desmethylclobazam AUC and Cmax are approximately 3-5 times higher in poor metabolizers (e.g., subjects with *2/*2 genotype) and 2 times higher in intermediate metabolizers (e.g., subjects with *1/*2 genotype). The prevalence of CYP2C19 poor metabolism differs depending on racial/ethnic background. Dosage in patients who are known CYP2C19 poor metabolizers may need to be adjusted [see Dosage and Administration (2.5)].

The systemic exposure of clobazam is similar for both CYP2C19 poor and extensive metabolizers.

13 NONCLINICAL TOXICOLOGY

13.1 Carcinogenesis, Mutagenesis, Impairment of Fertility

Carcinogenesis
In mice, oral administration of clobazam (0, 6, 12, or 24 mg/kg/day) for 2 years did not result in an increase in tumors. The highest dose tested was approximately 3 times the maximum recommended human dose (MRHD) of 40 mg/day, based on body surface area (mg/m^2).

In rats, oral administration of clobazam for 2 years resulted in increases in tumors of the thyroid gland (follicular cell adenoma and carcinoma) and liver (hepatocellular adenoma) at the mid and high doses. The low dose, not associated with an increase in tumors, was associated with plasma exposures (AUC) for clobazam and its major active metabolite, N-desmethylclobazam, less than that in humans at the MRHD.

Mutagenesis
Clobazam and the major active metabolite, N-desmethylclobazam, were negative for genotoxicity, based on data from a battery of in vitro (bacteria reverse mutation, mammalian clastogenicity) and in vivo (mouse micronucleus) assays.

Impairment of Fertility
In a fertility study in which clobazam (50, 350, or 750 mg/kg/day, corresponding to 12, 84, and 181 times the oral Maximum Recommended Human Dose, MRHD, of 40mg/day based on mg/m^2 body surface) was orally administered to male and female rats prior to and during mating and continuing in females to gestation day 6, increases in abnormal sperm and pre-implantation loss were observed at the highest dose tested. The no-effect level for fertility and early embryonic development in rats was associated with plasma exposures (AUC) for clobazam and its major active metabolite, N-desmethylclobazam, less than those in humans at the maximum recommended human dose of 40 mg/day.

14 CLINICAL STUDIES

14.1 Demonstration of Pharmacokinetic Equivalence Between SYMPAZAN® and Clobazam Tablets

The efficacy of SYMPAZAN® is based upon bioavailability studies comparing clobazam tablets to SYMPAZAN® [see Clinical Pharmacology (12.3)].

14.2 Adjunctive Treatment of Seizures Associated with Lennox-Gastaut Syndrome (LGS)

The effectiveness of clobazam for the adjunctive treatment of seizures associated with Lennox-Gastaut Syndrome was established in two multicenter controlled studies (Study 1 and Study 2). Both studies were similar in terms of disease characteristics and concomitant AED treatments. The most common concomitant AED treatments at baseline included: valproate, lamotrigine, levetiracetam, and topiramate.

Study 1
Study 1 (N=238) was a randomized, double-blind, placebo-controlled study consisting of a 4-week baseline period followed by a 3-week titration period and 12-week maintenance period. Patients age 2-54 years with a current or prior diagnosis of LGS were stratified into 2 weight groups (12.5 kg to ≤30 kg or >30 kg) and then randomized to placebo or one of three target maintenance doses of clobazam according to Table 4.

Table 4: Study 1 Total Daily Dose
 | ≤30 kg Body Weight | >30 kg Body Weight
Low Dose | 5 mg daily | 10 mg daily
Medium Dose | 10 mg daily | 20 mg daily
High Dose | 20 mg daily | 40 mg daily

Doses above 5 mg/day were administered in two divided doses.

The primary efficacy measure was the percent reduction in the weekly frequency of drop seizures (atonic, tonic, or myoclonic), also known as drop attacks, from the 4-week baseline period to 12-week maintenance period.

The pre-dosing baseline mean weekly drop seizure frequency was 98, 100, 61, and 105 for the placebo, low-, medium-, and high-dose groups, respectively. Figure 1 presents the mean percent reduction in weekly drop seizures from this baseline. All dose groups of clobazam were statistically superior (p≤0.05) to the placebo group. This effect appeared to be dose dependent.

Figure 1: Mean Percent Reduction from Baseline in Weekly Drop Seizure Frequency (Study 1)

Figure 2 shows changes from baseline in weekly drop seizure frequency by category for patients treated with clobazam and placebo in Study 1. Patients in whom the seizure frequency increased are shown at left as "worse." Patients in whom the seizure frequency decreased are shown in five categories.

Figure 2: Drop Seizure Response by Category for Clobazam and Placebo (Study 1)

There was no evidence that tolerance to the therapeutic effect of clobazam developed during the 3-month maintenance period.

Study 2
Study 2 (N=68) was a randomized, double-blind comparison study of high- and low-dose clobazam, consisting of a 4-week baseline period followed by a 3-week titration period and 4-week maintenance period. Patients age 2-25 years with a current or prior diagnosis of LGS were stratified by weight, then randomized to either a low or high dose of clobazam, and then entered a 3-week titration period.

The primary efficacy measure was the percent reduction in the weekly frequency of drop seizures (atonic, tonic, or myoclonic), also known as drop attacks, from the 4-week baseline period to the 4-week maintenance period.

A statistically significantly greater reduction in seizure frequency was observed in the high-dose group compared to the low-dose group (median percent reduction of 93% vs 29%; p<0.05).

16 HOW SUPPLIED/STORAGE AND HANDLING

Each SYMPAZAN® oral film is a white rectangular film that contains 5 mg, 10 mg or 20 mg of clobazam and printed in black ink either "C5,” "C10" or "C20" on the strip according to their respective strengths and each film is packaged in a pouch (sachet).

NDC 10094-205-60: 5 mg oral film, Package of 60

NDC 10094-210-60: 10 mg oral film, Package of 60

NDC 10094-220-60: 20 mg oral film, Package of 60

Store SYMPAZAN® oral film pouches (sachets) at 20°C to 25°C (68°F to 77°F); Excursions permitted to 15°C to 30°C (59°F to 86°F) [See USP controlled room temperature].

17 PATIENT COUNSELING INFORMATION

Advise the patient to read the FDA-approved patient labeling (Medication Guide and Instructions for Use).

Risks from Concomitant Use with Opioids

Inform patients and caregivers that potentially fatal additive effects may occur if SYMPAZAN® is used with opioids and not to use such drugs concomitantly unless supervised by a healthcare provider [see Warnings and Precautions (5.1), Drug Interactions (7.1)].

Abuse, Misuse, and Addiction

Inform patients that the use of SYMPAZAN, even at recommended dosages, exposes users to risks of abuse, misuse, and addiction, which can lead to overdose and death, especially when used in combination with other medications (e.g., opioid analgesics), alcohol, and/or illicit substances. Inform patients about the signs and symptoms of benzodiazepine abuse, misuse, and addiction; to seek medical help if they develop these signs and/or symptoms; and on the proper disposal of unused drug [see Warnings and Precautions (5.2) and Drug Abuse and Dependence (9.2)].

Withdrawal Reactions

Advise patients or caregivers that abrupt withdrawal of AEDs may increase their risk of seizure. Inform patients that the continued use of SYMPAZAN may lead to clinically significant physical dependence and that abrupt discontinuation or rapid dosage reduction of SYMPAZAN may precipitate acute withdrawal reactions, which can be life-threatening. Inform patients that in some cases, patients taking benzodiazepines have developed a protracted withdrawal syndrome with withdrawal symptoms lasting weeks to more than 12 months. Instruct patients that discontinuation or dosage reduction of SYMPAZAN may require a slow taper [see Warnings and Precautions (5.3) and Drug Abuse and Dependence (9.3)].

Somnolence or Sedation
Advise patients or caregivers to check with their healthcare provider before SYMPAZAN® is taken with other CNS depressants such as other benzodiazepines, opioids, tricyclic antidepressants, sedating antihistamines, or alcohol [see Warnings and Precautions (5.4, 5.5)].

If applicable, caution patients about operating hazardous machinery, including automobiles, until they are reasonably certain that SYMPAZAN® does not affect them adversely (e.g., impair judgment, thinking or motor skills).

Hypersensitivity

Inform patients or caregivers that SYMPAZAN® is contraindicated in patients with a history of hypersensitivity to the drug or its ingredients [see Warnings and Precautions (5.6)].

Interactions with Hormonal Contraceptives
Counsel women to also use non-hormonal methods of contraception when SYMPAZAN® is used with hormonal contraceptives and to continue these alternative methods for 28 days after discontinuing SYMPAZAN® to ensure contraceptive reliability [see Drug Interactions (7.3), Clinical Pharmacology (12.3)].

Serious Dermatological Reactions
Advise patients or caregivers that serious skin reactions have been reported in patients taking clobazam. Serious skin reactions, including SJS/TEN, may need to be treated in a hospital and may be life-threatening. If a skin reaction occurs while taking SYMPAZAN®, patients or caregivers should consult with healthcare providers immediately [see Warnings and Precautions (5.6)].

DRESS/Multiorgan Hypersensitivity

Instruct patients and caregivers that a fever or rash associated with signs of other organ system involvement (e.g., lymphadenopathy, hepatic dysfunction) may be drug-related and should be reported to their healthcare provider immediately. SYMPAZAN should be discontinued immediately if a serious hypersensitivity reaction is suspected [see Warnings and Precautions (5.7)].

Suicidal Thinking and Behavior
Counsel patients, their caregivers, and their families that AEDs, including SYMPAZAN®, may increase the risk of suicidal thoughts and behavior and advise them of the need to be alert for the emergence or worsening of symptoms of depression, any unusual changes in mood or behavior, or the emergence of suicidal thoughts, behavior, or thoughts of self-harm. Patients should report behaviors of concern immediately to healthcare providers [see Warnings and Precautions (5.8)].

Pregnancy

Advise pregnant females that the use of SYMPAZAN® late in pregnancy can result in in sedation (respiratory depression, lethargy, hypotonia) and/or withdrawal symptoms (hyperreflexia, irritability, restlessness, tremors, inconsolable crying, and feeding difficulties) in newborns [see Warnings and Precautions (5.9) and Use in Specific Populations (8.1)]. Instruct patients to notify their healthcare provider if they are pregnant.

Encourage patients to enroll in the North American Antiepileptic Drug (NAAED) Pregnancy Registry if they become pregnant while taking SYMPAZAN. The registry is collecting information about the safety of antiepileptic drugs during pregnancy [see Use in Specific Populations (8.1)].

Lactation

Counsel patients that clobazam, the active ingredient in SYMPAZAN®, is excreted in breast milk. Instruct patients to notify their healthcare provider if they are breast feeding or intend to breastfeed. Instruct breastfeeding patients who take SYMPAZAN to monitor their infants for excessive sedation, poor feeding and poor weight gain, and to seek medical attention if they notice these signs [see Use in Specific Populations (8.2)].

Manufactured by: Aquestive Therapeutics
Warren, NJ 07059

MEDICATION GUIDE
SYMPAZAN® (SYM-pa-zan)
(clobazam)
oral film, CIV

What is the most important information I should know about SYMPAZAN?

- SYMPAZAN is a benzodiazepine medicine. Taking benzodiazepines with opioid medicines, alcohol, or other central nervous system (CNS) depressants (including street drugs) can cause severe drowsiness, breathing problems (respiratory depression), coma, and death.
  Get emergency help right away if any of the following happens:
  ○ shallow or slowed breathing
  ○ breathing stops (which may lead to the heart stopping)
  ○ excessive sleepiness (sedation)
  Do not drive or operate heavy machinery until you know how taking SYMPAZAN with opioids affects you.
- Risk of abuse, misuse, and addiction. There is a risk for abuse, misuse, and addiction with benzodiazepines, including SYMPAZAN, which can lead to overdose and serious side effects including coma and death.
  ○ Serious side effects including coma and death have happened in people who have abused or misused benzodiazepines, including SYMPAZAN. These serious side effects may also include delirium, paranoia, suicidal thoughts or actions, seizures, and difficulty breathing. Call your healthcare provider or go to the nearest hospital emergency room right away if you get any of these serious side effects.
  ○ You can develop an addiction even if you take SYMPAZAN as prescribed by your healthcare provider.
  ○ Take SYMPAZAN exactly as your healthcare provider prescribed.
  ○ Do not share your SYMPAZAN with other people.
  ○ Keep SYMPAZAN in a safe place and away from children.
- Physical dependence and withdrawal reactions. SYMPAZAN can cause physical dependence and withdrawal reactions.
  ○ Do not suddenly stop taking SYMPAZAN. Stopping SYMPAZAN suddenly can cause serious and life-threatening side effects, including, unusual movements, responses, or expressions, seizures, sudden and severe mental or nervous system changes, depression, seeing or hearing things that others do not see or hear, an extreme increase in activity or talking, losing touch with reality, and suicidal thoughts or actions. Call your healthcare provider or go to the nearest hospital emergency room right away if you get any of these symptoms.
  ○ Some people who suddenly stop benzodiazepines have symptoms that can last for several weeks to more than 12 months, including, anxiety, trouble remembering, learning, or concentrating, depression, problems sleeping, feeling like insects are crawling under your skin, weakness, shaking, muscle twitching, burning, or prickling feeling in your hands, arms, legs or feet, and ringing in your ears.
  ○ Physical dependence is not the same as drug addiction. Your healthcare provider can tell you more about the differences between physical dependence and drug addiction.
  ○ Do not take more SYMPAZAN than prescribed or take SYMPAZAN for longer than prescribed.
- SYMPAZAN can make you sleepy or dizzy and can slow your thinking and motor skills.
  ○ Do not drive, operate heavy machinery, or do other dangerous activities until you know how SYMPAZAN affects you.
  ○ Do not drink alcohol or take other drugs that may make you sleepy or dizzy while taking SYMPAZAN without first talking to your healthcare provider. When taken with alcohol or drugs that cause sleepiness or dizziness, SYMPAZAN may make your sleepiness or dizziness much worse.
- Serious skin reactions have been seen when SYMPAZAN is taken with other medicines and may require stopping its use. Do not stop taking SYMPAZAN without first talking to your healthcare provider.
  ○ A serious skin reaction can happen at any time during your treatment with SYMPAZAN, but is more likely to happen within the first 8 weeks of treatment. These skin reactions may need to be treated right away.
  ○ Call your healthcare provider immediately if you have skin blisters, rash, sores in mouth, hives or any other allergic reaction.
- A serious allergic reaction that may affect your skin or other parts of your body such as your liver, kidneys, heart, or blood cells.This allergic reaction can be life-threatening and can cause death, particularly if it is not treated as early as possible. Call your healthcare provider right away if you have:
  ○ a skin rash ○ fever or swollen glands that do not go away
  ○ swelling of your face ○ shortness of breath
  ○ dark urine ○ yellowing of the skin or whites of the eyes

- Like other antiepileptic medicines, SYMPAZAN may cause suicidal thoughts or actions in a very small number of people, about 1 in 500.

Call your healthcare provider right away if you have any of these symptoms, especially if they are new, worse, or worry you:

○ thoughts about suicide or dying

○ attempts to commit suicide

○ new or worse depression

○ new or worse anxiety or irritability

○ feeling agitated or restless

○ an extreme increase in activity and talking (mania)

○ trouble sleeping (insomnia)

○ new or worse panic attacks

○ acting aggressive, being angry or violent

○ acting on dangerous impulses

○ other unusual changes in behavior or mood

How can I watch for early symptoms of suicidal thoughts and actions?

- Pay attention to any changes, especially sudden changes, in mood, behaviors, thoughts, or feelings.
- Keep all follow-up visits with your healthcare provider as scheduled.

Call your healthcare provider between visits as needed, especially if you are worried about symptoms.
Stopping a seizure medicine suddenly in a patient who has epilepsy can cause seizures that will not stop (status epilepticus).
Suicidal thoughts or actions can be caused by things other than medicines. If you have suicidal thoughts or actions, your healthcare provider may check for other causes.

What is SYMPAZAN?

- SYMPAZAN is a prescription medicine used along with other medicines to treat seizures associated with Lennox-Gastaut Syndrome in people 2 years of age or older.
- SYMPAZAN is a federally controlled substance (C-IV) because it contains clobazam that can be abused or lead to dependence. Keep SYMPAZAN in a safe place to prevent misuse and abuse. Selling or giving away SYMPAZAN may harm others, and is against the law. Tell your healthcare provider if you have ever abused or been dependent on alcohol, prescription medicines or street drugs.

It is not known if SYMPAZAN is safe and effective in children less than 2 years old.

Do not take SYMPAZAN if you:

- are allergic to clobazam or any of the ingredients in SYMPAZAN. See the end of this Medication Guide for a complete list of ingredients in SYMPAZAN.

Before you take SYMPAZAN, tell your healthcare provider about all of your medical conditions, including if you:

- have liver or kidney problems
- have lung problems (respiratory disease)
- have or have had depression, mood problems, or suicidal thoughts or behavior
- use birth control medicine. SYMPAZAN may cause your birth control medicine to be less effective. Talk to your healthcare provider about the best birth control method to use.
- are pregnant or plan to become pregnant.
  o Taking SYMPAZAN late in pregnancy may cause your baby to have symptoms of sedation (breathing
  problems, sluggishness, low muscle tone) and/or withdrawal symptoms (jitteriness, irritability,
  restlessness, shaking, excessive crying, feeding problems).
  o Tell your healthcare provider right away if you become pregnant or think you are pregnant during
  treatment with SYMPAZAN.
  o If you become pregnant while taking SYMPAZAN, talk to your healthcare provider about registering
  with the North American Antiepileptic Drug Pregnancy Registry. You can register by calling 1-888-
  233-2334. For more information about the registry go to http://www.aedpregnancyregistry.org. The
  purpose of this registry is to collect information about the safety of antiepileptic drugs during
  pregnancy.
- Are breastfeeding or plan to breastfeed. SYMPAZAN can pass into breast milk.
  o Breastfeeding during treatment with SYMPAZAN may cause your baby to have sleepiness, feeding
  problems, and decreased weight gain.
  o Talk to your healthcare provider about the best way to feed your baby if you take SYMPAZAN.

Tell your healthcare provider about all the medicines you take, including prescription and over-the counter medicines, vitamins, and herbal supplements. Taking SYMPAZAN with certain other medicines can cause side effects or affect how well SYMPAZAN or the other medicines work. Do not start or stop other medicines without talking to your healthcare provider.

How should I take SYMPAZAN?

- Take SYMPAZAN exactly as your healthcare provider tells you to take it.
- Your healthcare provider will tell you how much SYMPAZAN to take and when to take it.
- Place the entire SYMPAZAN oral film on top of the tongue.
- SYMPAZAN oral films can be taken with or without food.
- Do not take liquids with SYMPAZAN oral films.
- Take only 1 SYMPAZAN oral film at a time.
- Read the Instructions for Use at the end of this Medication Guide for information on the right way to take SYMPAZAN oral films.
- Your healthcare provider may change your dose if needed. Do not change your dose of SYMPAZAN without talking to your healthcare provider.
- Do not stop taking SYMPAZAN without first talking to your healthcare provider.
- Stopping SYMPAZAN suddenly can cause serious problems.
- If you take too much SYMPAZAN, call your healthcare provider or go to the nearest hospital emergency room right away.

What should I avoid while taking SYMPAZAN?
See “What is the most important information I should know about SYMPAZAN?”

What are the possible side effects of SYMPAZAN?
SYMPAZAN may cause serious side effects, including:

- See "What is the most important information I should know about SYMPAZAN?"

The most common side effects of SYMPAZAN include:

● sleepiness

● drooling

● constipation

● cough

● pain with urination

● fever

● acting aggressive, being angry, or violent

● difficulty sleeping

● slurred speech

● tiredness

● problems with breathing

These are not all the possible side effects of SYMPAZAN. Call your doctor for medical advice about side effects. You may report side effects to FDA at 1-800-FDA-1088.

How should I store SYMPAZAN?

- Store SYMPAZAN oral film at room temperature between 68°F to 77°F (20°C to 25°C).

Keep SYMPAZAN and all medicines out of the reach of children.

General Information about the safe and effective use of SYMPAZAN.
Medicines are sometimes prescribed for purposes other than those listed in a Medication Guide. Do not use SYMPAZAN for a condition for which it was not prescribed. Do not give SYMPAZAN to other people, even if they have the same symptoms that you have. It may harm them. You can ask your pharmacist or healthcare provider for information about SYMPAZAN that is written for health professionals.

What are the ingredients in SYMPAZAN?
Active ingredient: clobazam
Inactive ingredients: artificial cooling flavor, citric acid, glycerol monooleate, hypromellose, maltitol, natural and artificial bitter masker, natural raspberry type flavor, polyethylene oxide, purified water, sodium phosphate dibasic, and sucralose.
Manufactured by:
Aquestive Therapeutics
Warren, NJ 07059
SYMPAZAN® is a registered trademark of Aquestive Therapeutics
For more information, go to www.SYMPAZAN.com or call 1-800-518-1084

This Medication Guide has been approved by the U.S. Food and Drug Administration Revised: 3/2024

PATIENT INFORMATION

Instructions for Use

SYMPAZAN® (SIM-pa-zan)

(clobazam) oral film, CIV

Read this Instructions for Use before you start using SYMPAZAN and each time you get a refill. There may be new information. The information does not take the place of talking with your healthcare provider about your medical condition or treatment.

Important Information for Patient and Caregiver:

- Do not take SYMPAZAN until:
  ○ you have read and understand these instructions.
  ○ you have reviewed the steps with your healthcare provider on how to take it.
  ○ you know the right time, how often, and the dose to take.
  ○ you feel comfortable with how to use SYMPAZAN.
- If you are not sure about giving treatment or when to give treatment, call your healthcare provider before using SYMPAZAN.

How should I store SYMPAZAN?

- Store SYMPAZAN at room temperature between 68°F to 77°F (20°C to 25°C).
- Keep SYMPAZAN in the foil pouch until you are ready to use. Use right away after opening foil pouch.
- Keep SYMPAZAN and all medicines out of the reach of children.

How to Use SYMPAZAN:

- Take only 1 SYMPAZAN film at a time unless instructed differently by your healthcare provider. If a second film is needed to get a full dose of SYMPAZAN, do not take the second film until the first film has completely dissolved.
- Place the entire SYMPAZAN oral film on top of the tongue. Check your prescription or contact your healthcare provider if you are not sure about the amount to take.
- Make sure your hands are clean and dry before handling the SYMPAZAN film.
- Check the expiration date printed on the foil pouch. Do not use SYMPAZAN if expired.

Step 1. Open Pouch

- Fold foil pouch along solid line.
- Note where the slit is and carefully tear it to open pouch.

Step 2. Remove Film

- Remove the SYMPAZAN from the foil pouch.

Step 3. Place on Tongue

- Place SYMPAZAN on top of the tongue. The film will stick to the tongue and begin to dissolve.

Step 4. Close Mouth and Swallow Saliva Normally

- Close mouth.
- Swallow saliva normally as SYMPAZAN dissolves.
- Do not take with liquids.
- Do not chew, spit, or talk while SYMPAZAN dissolves.

- Wash your hands after taking SYMPAZAN.
- Throw away the empty foil pouch in the regular trash.

Manufactured by:
Aquestive Therapeutics
Warren, NJ 07059

For more information or support about SYMPAZAN: Call 1-800-518-1084

This Instructions for Use has been approved by the U.S. Food and Drug Administration. Revision Date: 11/2018

PRINCIPAL DISPLAY PANEL

NDC 10094-205-01
Sympazan
(clobazam) Oral film
5 mg
Rx Only
1 Oral films

PRINCIPAL DISPLAY PANEL

NDC 10094-205-60
Sympazan
(clobazam) Oral film
5 mg
Rx Only
60 Oral films

PRINCIPAL DISPLAY PANEL

NDC 10094-210-01
Sympazan
(clobazam) Oral film
10 mg
Rx Only
1 Oral films

PRINCIPAL DISPLAY PANEL

NDC 10094-210-60
Sympazan
(clobazam) Oral film
10 mg
Rx Only
60 Oral films

PRINCIPAL DISPLAY PANEL

NDC 10094-220-01
Sympazan
(clobazam) Oral film
20 mg
Rx Only
1 Oral films

PRINCIPAL DISPLAY PANEL

NDC 10094-220-60
Sympazan
(clobazam) Oral film
20 mg
Rx Only
60 Oral films